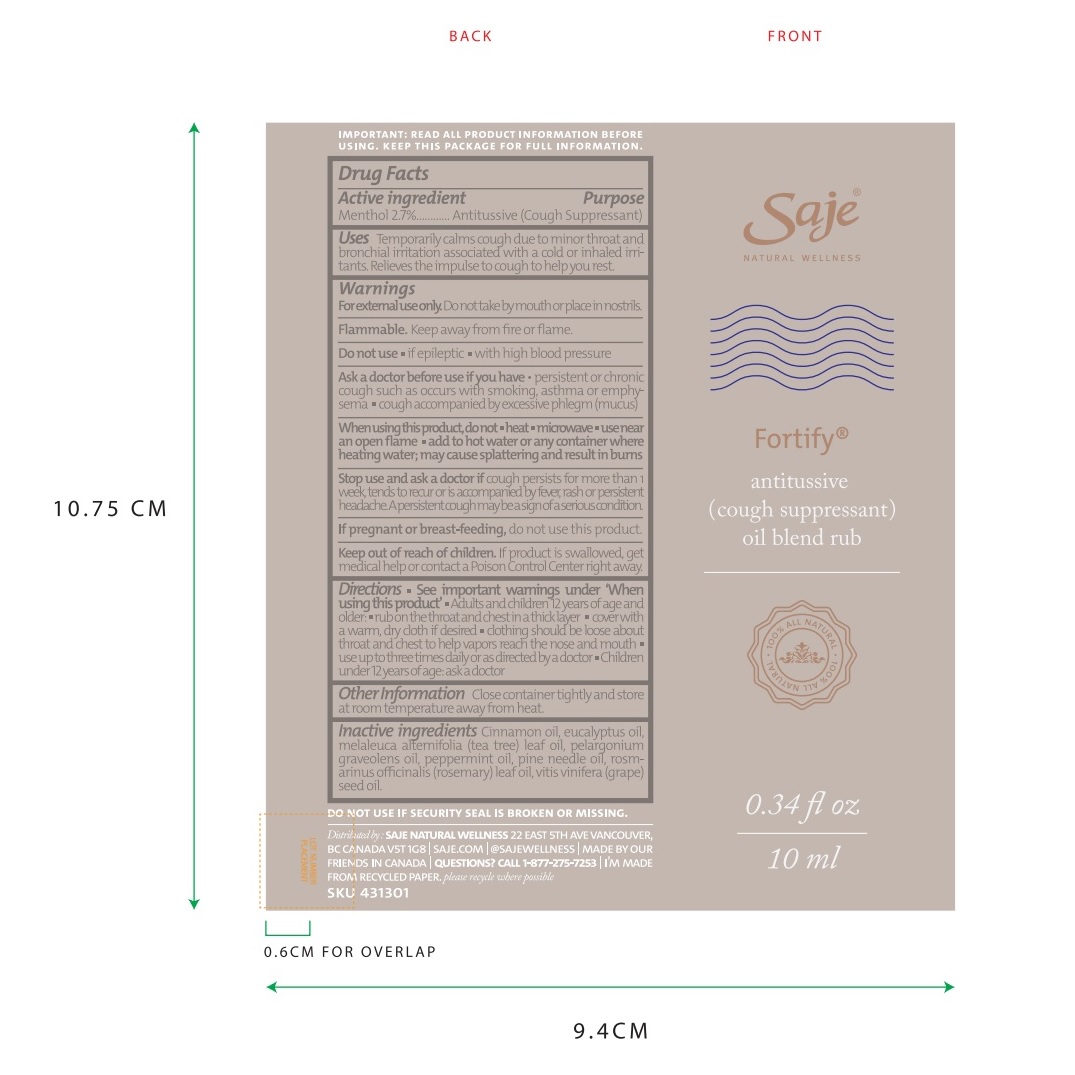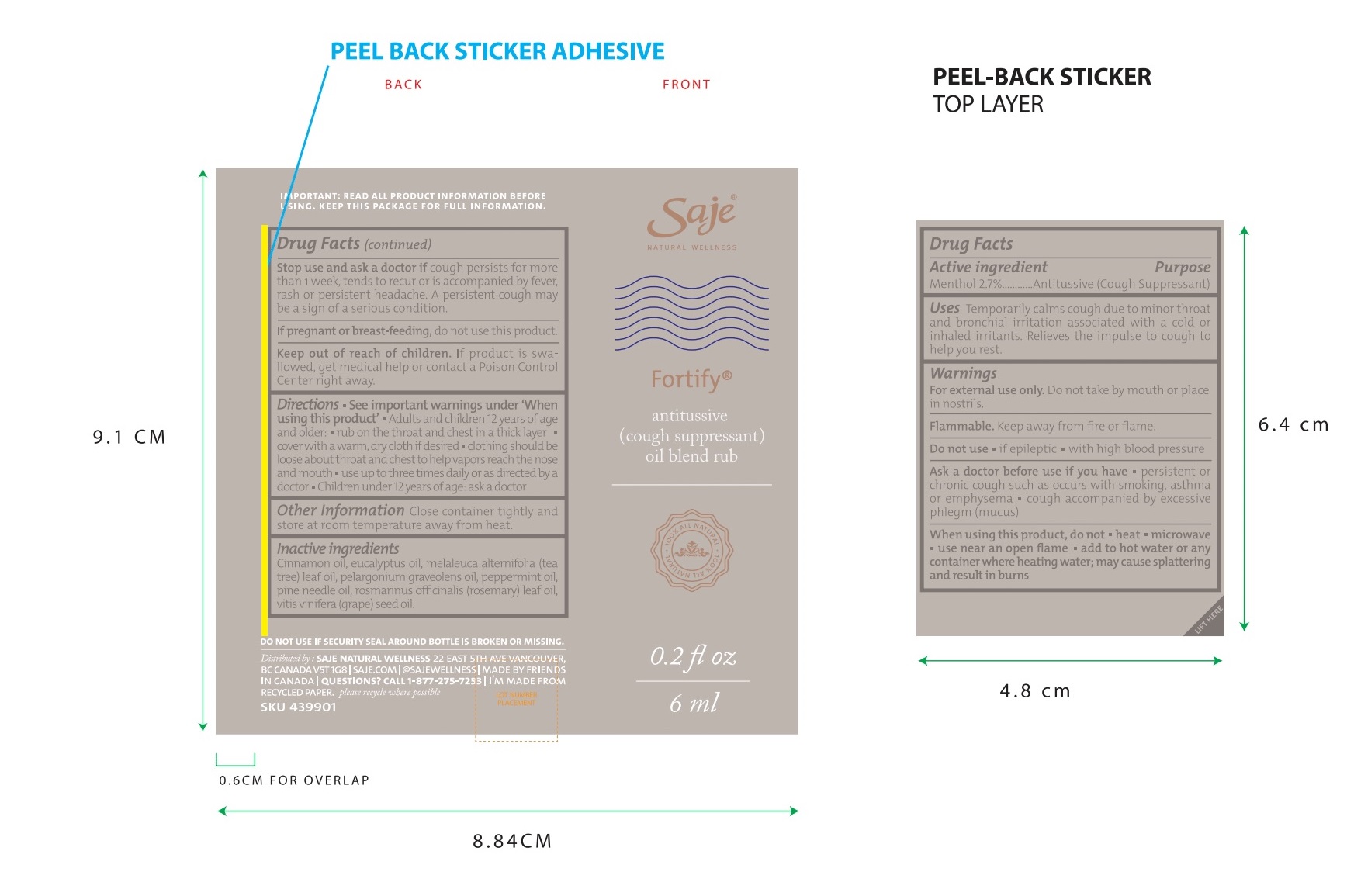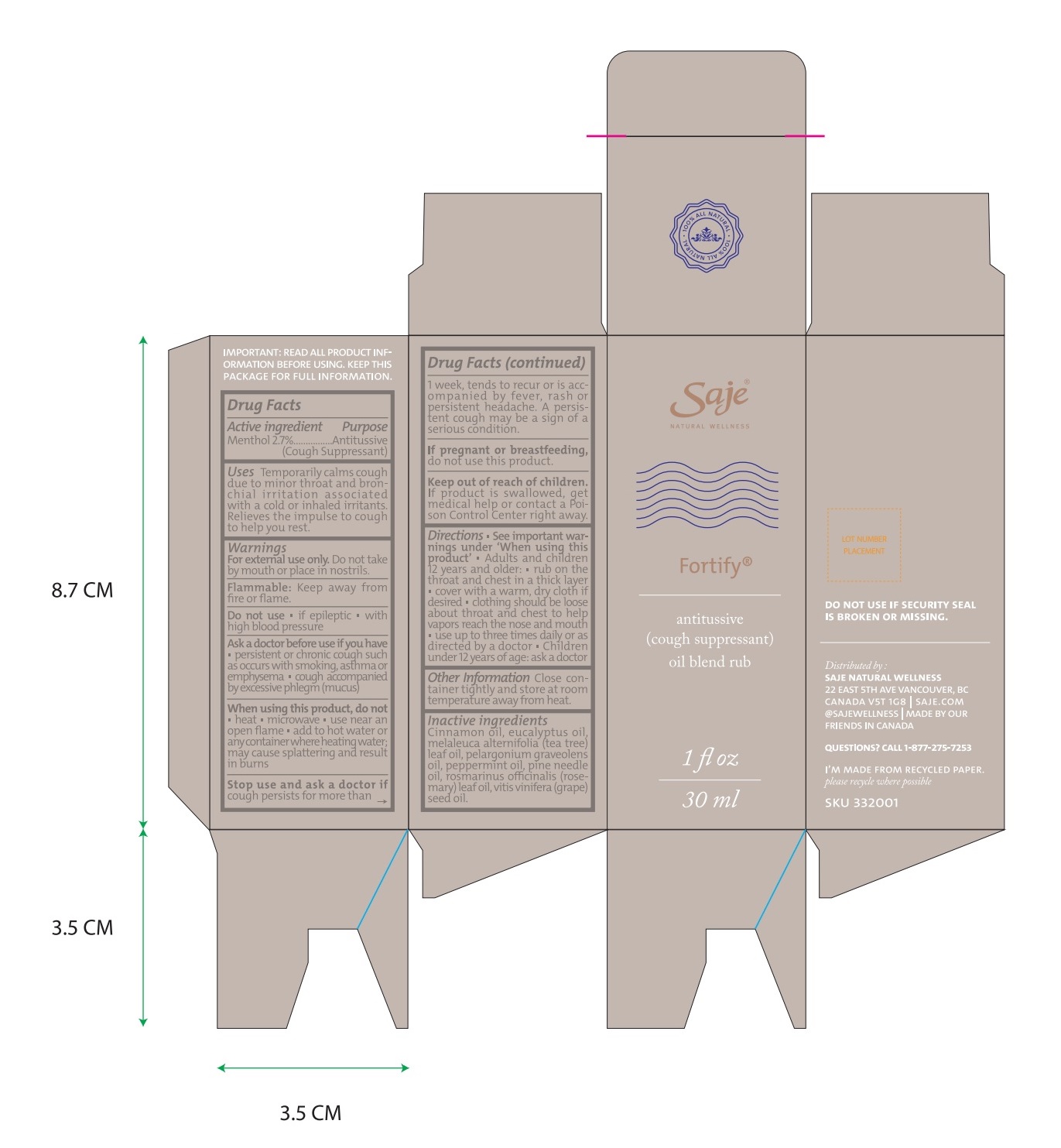 DRUG LABEL: Fortify
NDC: 70983-002 | Form: OIL
Manufacturer: Saje Natural Business Inc.
Category: otc | Type: HUMAN OTC DRUG LABEL
Date: 20260113

ACTIVE INGREDIENTS: MENTHOL 24 mg/1 mL
INACTIVE INGREDIENTS: CINNAMON OIL; EUCALYPTUS OIL; TEA TREE OIL; PELARGONIUM GRAVEOLENS FLOWER OIL; PEPPERMINT OIL; PINE NEEDLE OIL (PINUS SYLVESTRIS); ROSEMARY OIL; GRAPE SEED OIL

Fortify Antitussive (Cough Suppressant) Oil Blend Rub (30 ml, 10 ml, 6 ml)

IMPORTANT: READ ALL PRODUCT INFORMATION BEFORE USING. KEEP THIS PACKAGE FOR FULL INFORMATION.

DRUG FACTS Active ingredient

Menthol 2.7%

Purpose Antitussive (Cough Suppressant)

Uses Temporarily calms cough due to minor throat and bronchial irritation associated with a cold or inhaled irritants. Relieves the impulse to cough to help you rest.

Warnings

For external use only.

Do not take by mouth or place in nostrils

Flammable: Keep away from fire or flame.

Do not use

- if epileptic
- with high blood pressure

Ask a doctor before use if you have

- persistent or chronic cough such as occurs with smoking, asthma, or emphysema
- cough accompanied by excessive phlegm (mucus).

When using this product, do not

- heat
- microwave
- use near an open flame
- add to hot water or any container where heating water. May cause splattering and result in burns.

Stop use and ask a doctor if

cough persists for more than 1 week, tends to recur, or is accompanied by fever, rash, or persistent headache. A persistent cough may be a sign of a serious condition.

If pregnant or breast-feeding,

do not use this product.

Keep out of reach of children.

If product is swallowed, get medical help or contact a Poison Control Center right away.

Directions

- See important warnings under 'When using this product'.
- Adults and children 12 years of age and older: rub on the throat and chest in a thick layer
- cover with a warm, dry cloth if desired
- clothing should be loose about throat and chest to help vapors reach the nose and mouth

DOSAGE AND ADMINISTRATION

- use up to three times daily or as directed by a doctor.
- Children under 12 years of age: ask a doctor.

Other information

- Close container tightly and store at room temperature away from heat

Inactive ingredients

Cinnamon oil, eucalyptus oil, melaleuca alternifolia (tea tree) leaf oil, pelargonium graveolens oil, peppermint oil, pine needle oil, rosmarinus officinalis (rosemary) leaf oil, and vitis vinifera (grape) seed oil.

Questions?

1-877-275-7253

Distributed by: SAJE NATURAL WELLNESS 22 East 5th Ave. Vancouver, BC Canada V5T 1G8 | saje.com | @sajewellness | 1-877-275-7253 | Made in Canada

Do not use if security seal around bottle is broken or missing.

Fortify 30 ml

SKU 332001

Fortify 10 ml

SKU 431301

Fortify 6 ml

SKU 439901

DISPOSAL AND WASTE HANDLING

Please recycle where possible.

Fortify Antitussive (Cough Suppressant) Oil Blend Rub - 30 ml

Saje® Natural Wellness

Fortify

Antitussive (Cough Suppressant) Oil Blend Rub

1 fl. oz. | 30 ml

Fortify Antitussive (Cough Suppressant) Oil Blend Rub - 10 ml

Saje® Natural Wellness

Fortify

Antitussive (Cough Suppressant) Oil Blend Rub

0.34 fl. oz. | 10 ml

Fortify Antitussive (Cough Suppressant) Oil Blend Rub - 6 ml

Saje® Natural Wellness

Fortify

Antitussive (Cough Suppressant) Oil Blend Rub

0.2 fl. oz. | 6 ml